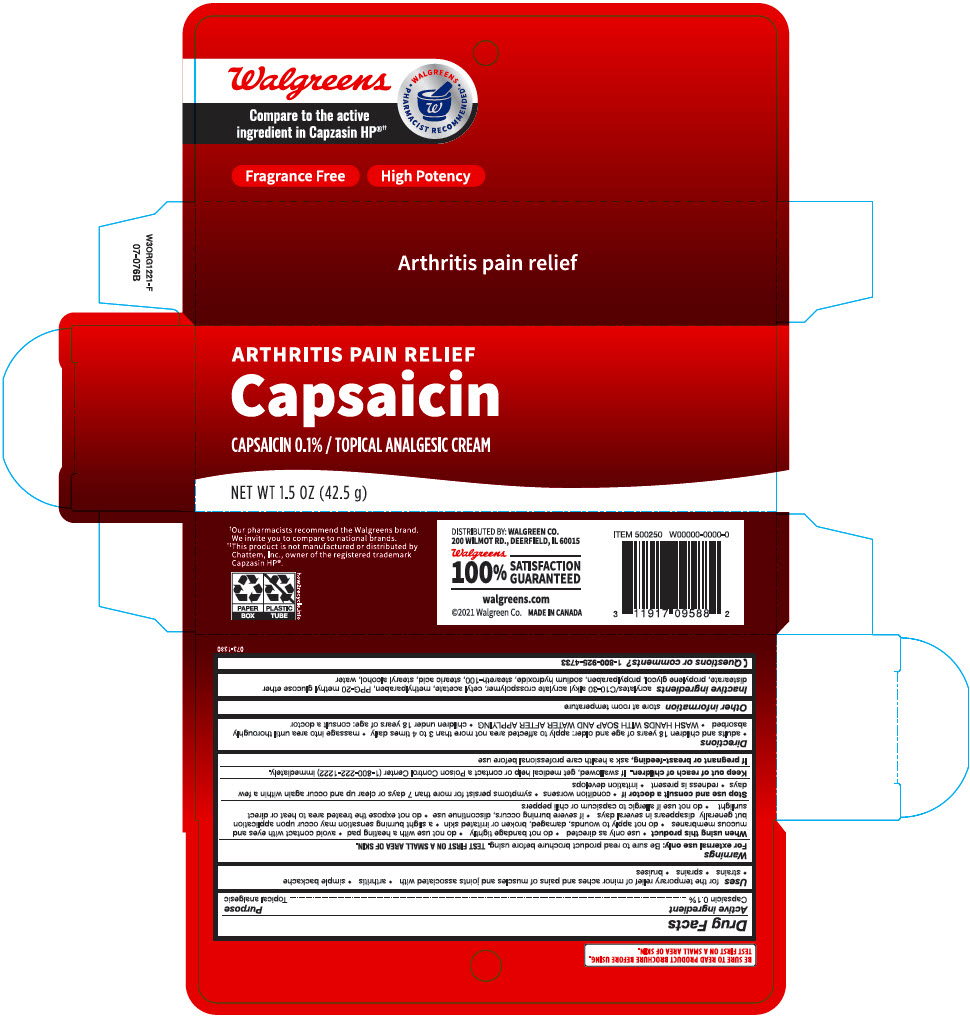 DRUG LABEL: Walgreens Arthritis Pain Relief Capsaicin Analgesic
NDC: 0363-0837 | Form: CREAM
Manufacturer: Walgreen Company
Category: otc | Type: HUMAN OTC DRUG LABEL
Date: 20241030

ACTIVE INGREDIENTS: Capsaicin 1 mg/1 g
INACTIVE INGREDIENTS: CARBOMER INTERPOLYMER TYPE A (ALLYL SUCROSE CROSSLINKED); Cetyl Acetate; METHYLPARABEN; PPG-20 Methyl Glucose Ether Distearate; Propylene Glycol; Propylparaben; Sodium Hydroxide; Steareth-100; Stearic Acid; STEARYL ALCOHOL; Water

Walgreens Arthritis Pain Relief Capsaicin Topical Analgesic Cream

Drug Facts

Active ingredient

Capsaicin 0.1%

Purpose

Topical Analgesic

Uses

for the temporarily relief of minor aches and pains of muscles and joints associated with

- arthritis
- simple backache
- strains
- sprains
- bruises

Warnings

For external use only: Be sure to read product brochure before using. TEST FIRST ON SMALL AREA OF SKIN.

When using this product

- use only as directed
- do not bandage tightly
- do not use with a heating pad
- avoid contact with eyes and mucous membranes
- do not apply to wounds, damaged, broken or irritated skin
- a slight burning sensation may occur upon application but generally disappears in several days
- if severe burning occurs, discontinue use
- do not expose the treated area to heat or direct sunlight
- do not use if allergic to capsicum or chili peppers

Stop use and consult a doctor if

- condition worsens
- symptoms persist for more than 7 days or clear up and occur again within a few days
- redness is present
- irritation develops

Keep out of reach of children. If swallowed, get medical help or contact a Poison Control Center (1-800-222-1222) immediately.

PREGNANCY OR BREAST FEEDING

If pregnant or breast- feeding, ask a health care professional before use

Directions

- adults and children 18 years of age and older: apply to affected area not more than 3 to 4 times daily
- massage into area until thoroughly absorbed
- WASH HANDS WITH SOAP AND WATER AFTER APPLYING
- children under 18 years of age: consult a doctor

Other information

store at room temperature

Inactive ingredients

acrylates/C10-30 slkyl acrylate crosspolymer, cetyl acetate, methylparaben, PPG-20 methyl glucose ether distearate, propylene glycol, propylparaben, sodium hydroxide, steareth-100, stearic acid, stearyl alcohol, water

Questions or comments?

1-800-925-4733

DISTRIBUTED BY: WALGREEN CO.
200 WILMOT RD., DEERFIELD, IL 60015

PRINCIPAL DISPLAY PANEL - 42.5 g Tube Carton

ARTHRITIS PAIN RELIEF
Capsaicin

CAPSAICIN 0.1% / TOPICAL ANALGESIC CREAM

NET WT 1.5 OZ (42.5 g)